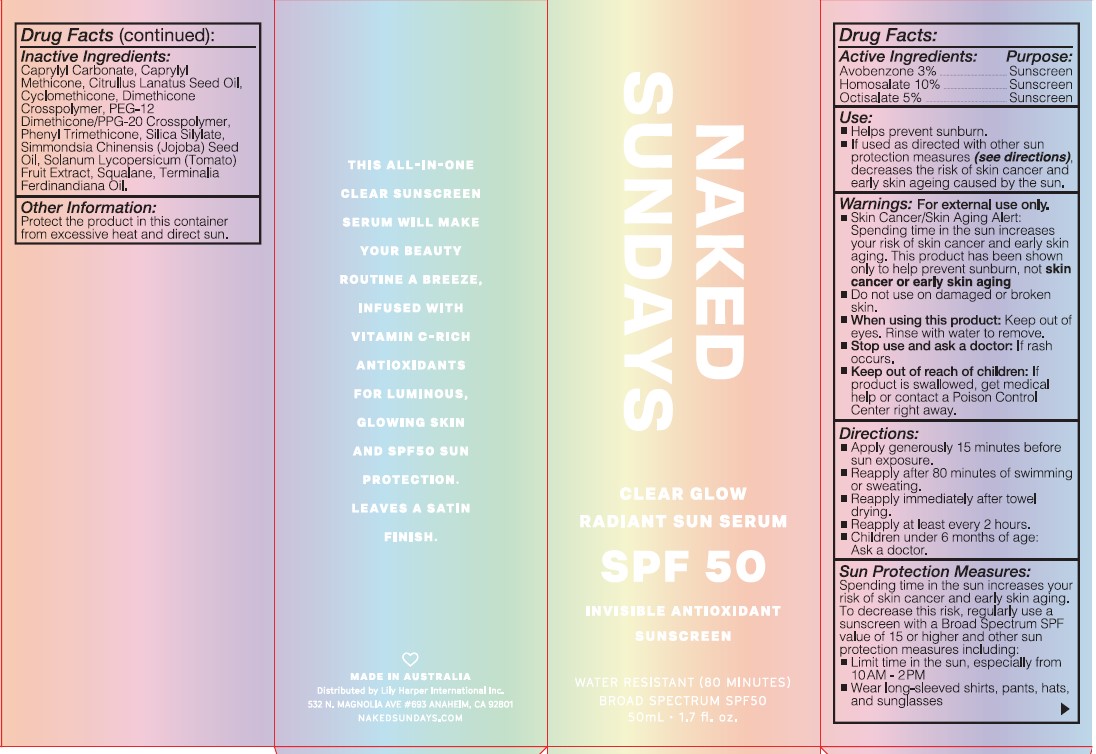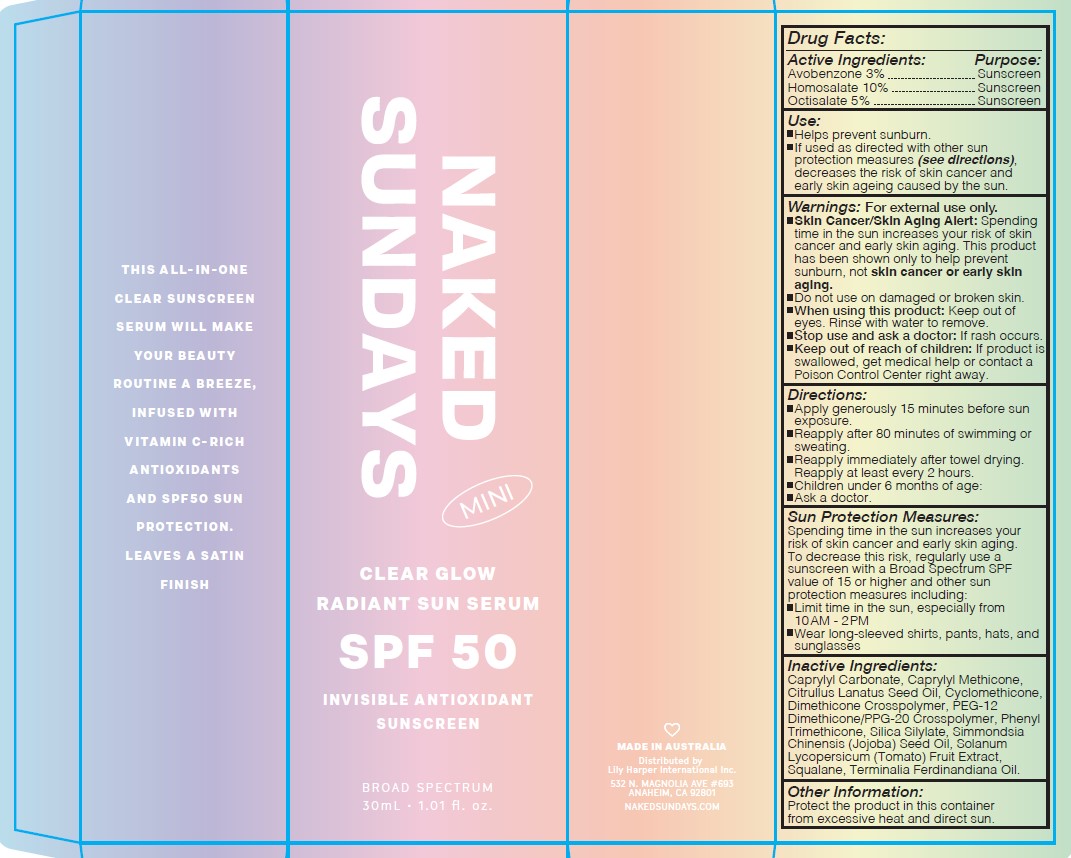 DRUG LABEL: CLEAR GLOW RADIANT SUN SERUM
NDC: 81104-112 | Form: LOTION
Manufacturer: NAKED SUNDAYS PTY LTD
Category: otc | Type: HUMAN OTC DRUG LABEL
Date: 20250722

ACTIVE INGREDIENTS: AVOBENZONE 3 g/100 mL; HOMOSALATE 10 g/100 mL; OCTISALATE 5 g/100 mL
INACTIVE INGREDIENTS: DICAPRYLYL CARBONATE; SQUALANE; KAKADU PLUM; TOMATO JUICE; SILICA DIMETHYL SILYLATE; PHENYL TRIMETHICONE; PEG-12 DIMETHICONE/PPG-20 CROSSPOLYMER; JOJOBA OIL; CAPRYLYL TRISILOXANE; WATERMELON SEED OIL; CYCLOMETHICONE; DIMETHICONE CROSSPOLYMER (450000 MPA.S AT 12% IN CYCLOPENTASILOXANE); POLYETHYLENE GLYCOL 600

NAKED SUNDAYS CLEAR GLOW RADIANT SUN SERUM SPF50

ACTIVE INGREDIENTS

AVOBENZONE 3 %

HOMOSALATE 10%

OCTISALATE 5 %

PURPOSE

SUNSCREEN

USE

- Helps prevents sunburn

- If used as directed with other sun protection measures (see directions) decreases the risk of skin cancer and early skin ageing caused by the sun.

WARNINGS

FOR EXTERNAL USE ONLY

Skin Cancer/Skin Aging alert: spending time in the sun increases your risk of skin cancer and early skin aging. This Product has been shown only to help prevent sunburn, not skin cancer or early skin aging

- Do not use on damaged or broken skin.

WHEN USING

keep out of eyes, Rinse with water to remove

Stop use & ask doctor

If rash occurs

KEEP OUT OF REACH OF CHILDREN

If product is swallowed , get medical help or contact a poison control center right away

Directions

- Apply 15 minutes before sun exposure

- reapply after 80 minutes of swimming or sweating

- Re-apply immedieatly after towel drying

- Re-apply at least every 2 hours

- Children under 6 months of age- ask a doctor

Sun Protection Measures :

Spending time in the sun increases your risk of skin cancer and early skin aging. To decrease this risk, regularly use a sunscreen with a Broad spectrum SPF value of 15 or higher and other sun protection measures inclusing:

- limit time in the sun, especially from 10:00 AM- 02:00 PM

- Wear long- Sleeved shirts , pants, Hats and sunglasses

Ingredients

caprylyl carbonate,caprylyl Methicone, Citrullus Lanatus Seed Oil, Cyclomethicone,Dimethicone crosspolymer, PEG-12 demithicone/PPG-20 Crosspolymer, Phenyl Trimethicone, Silica Silylate, Simmondsia chinensis (jojoba) seed oil, Solanum Lycopersicum (tomato)fruit extract,Squalane, terminalia ferdinadiana oil

OTHER SAFETY INFORMATION

Protect the product in this container from excessive heat & direct sun

DOSAGE AND ADMINISTRATION

Apply 15 minutes before skin exposure